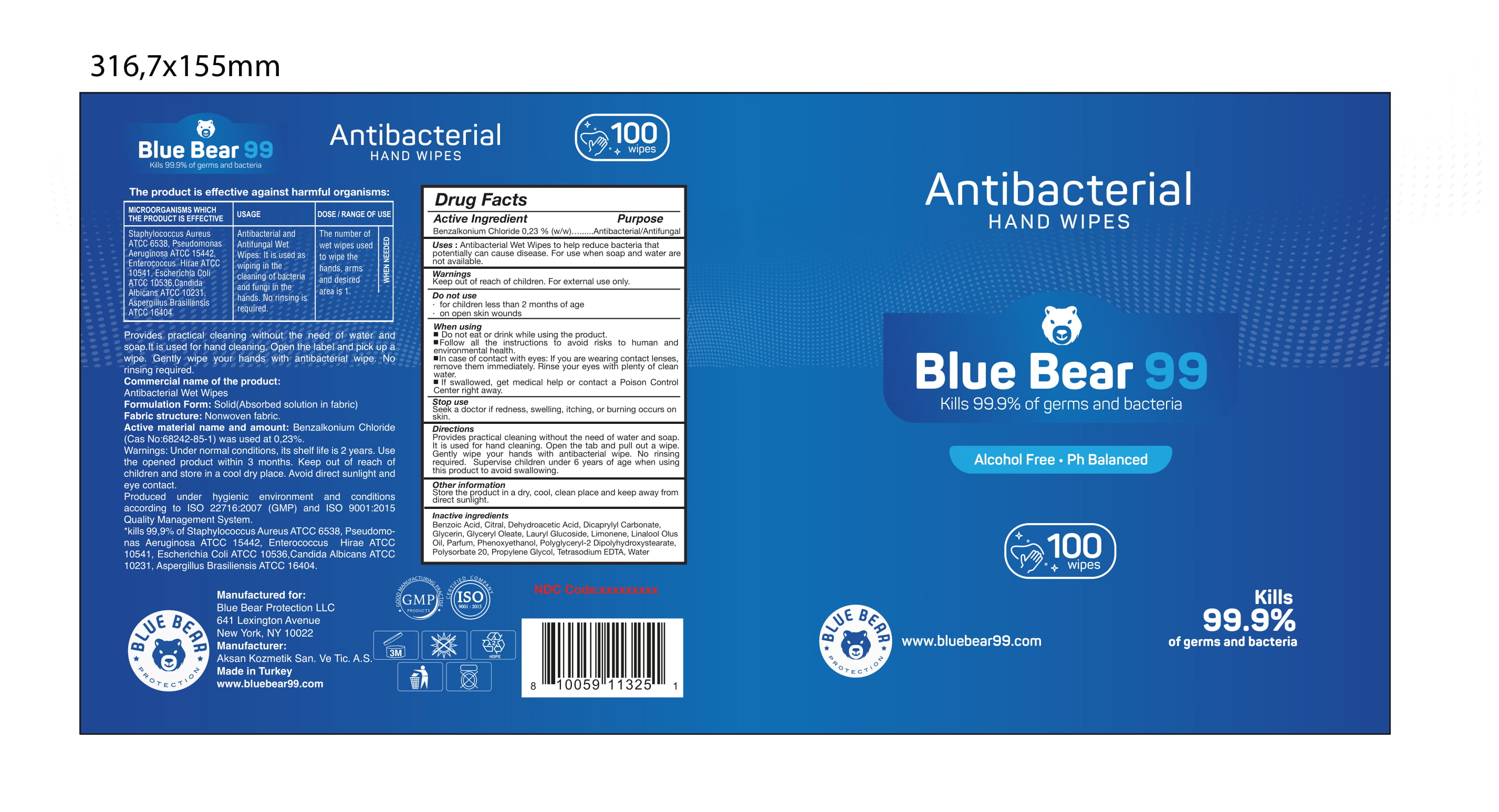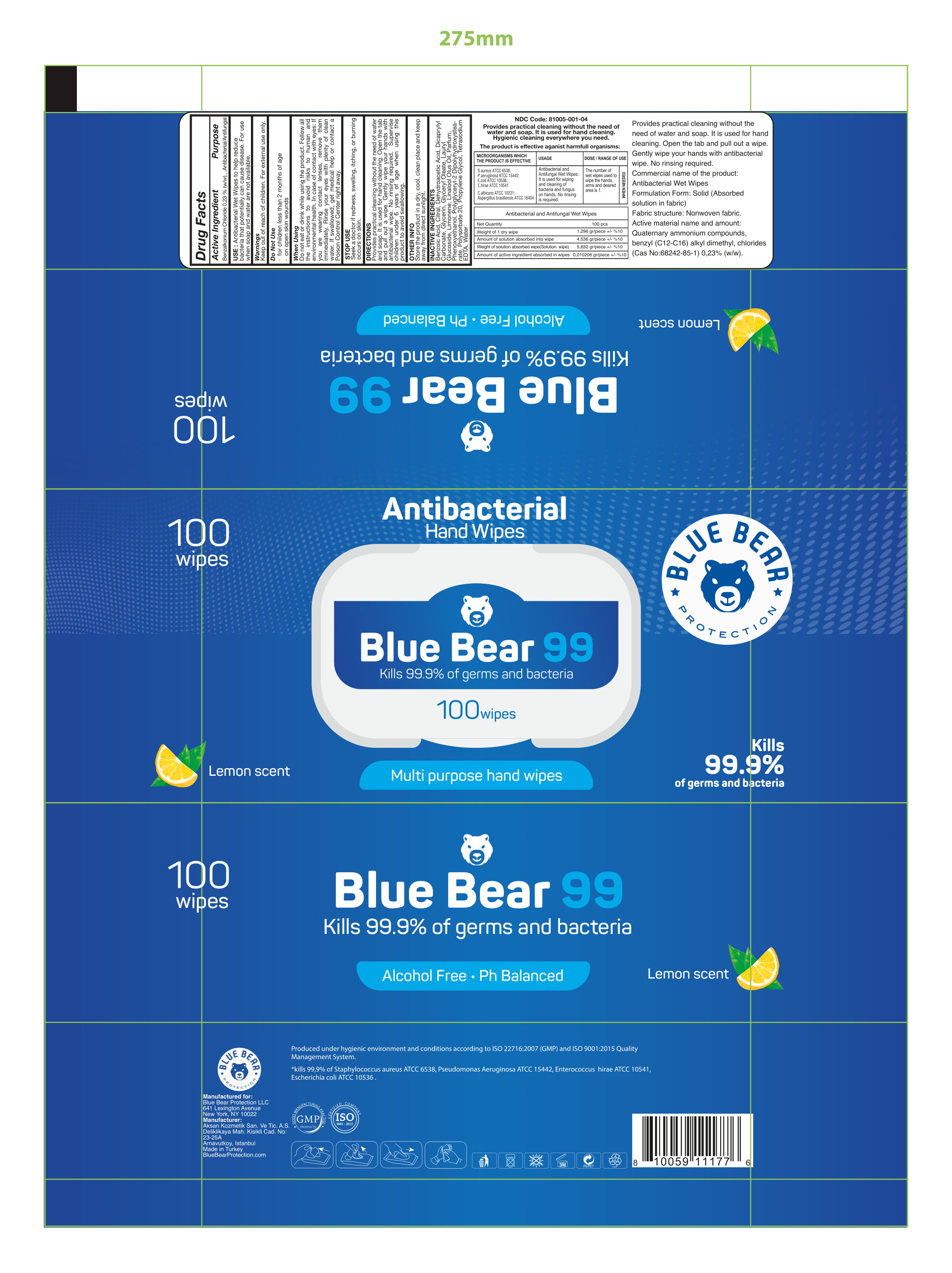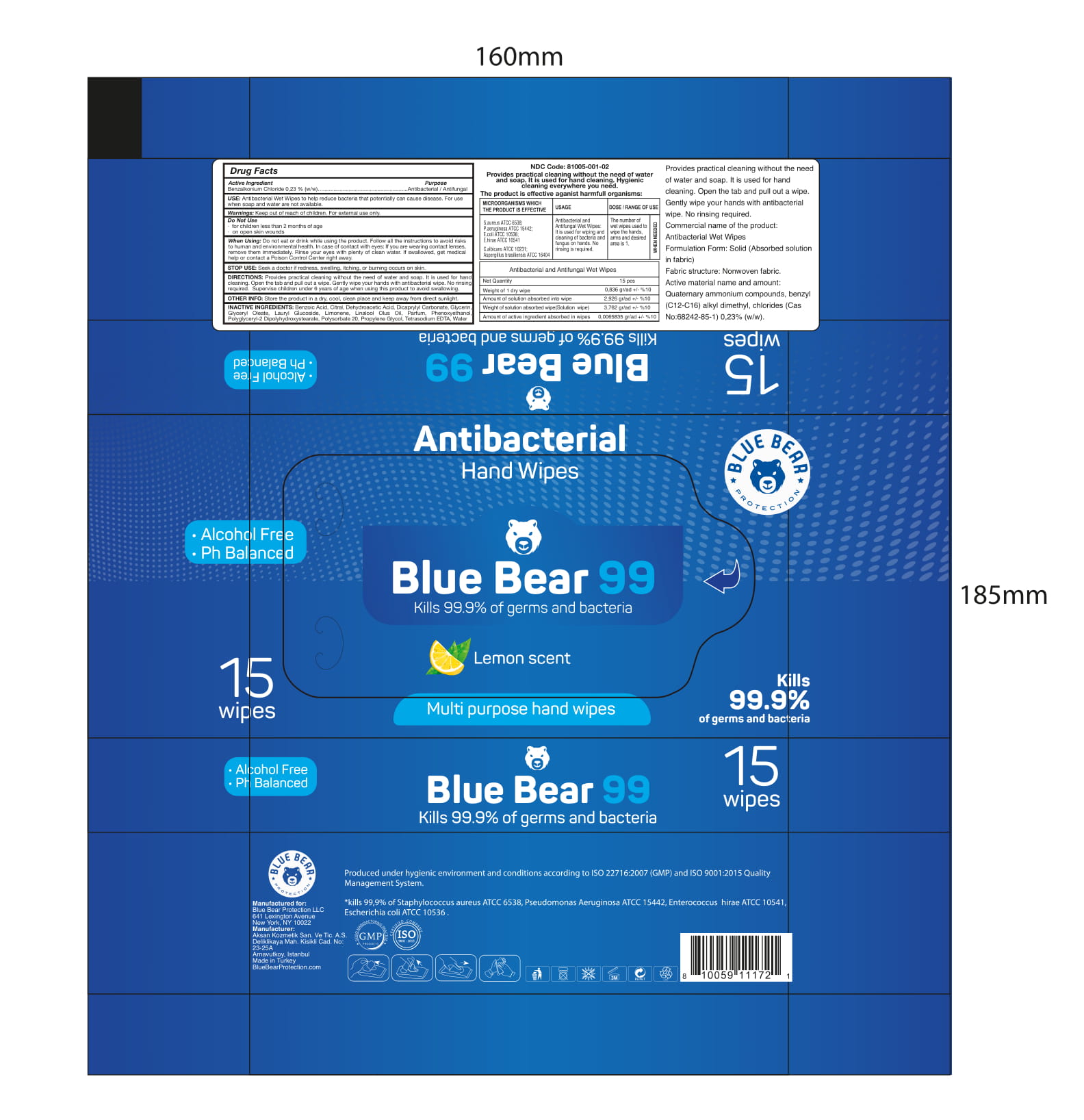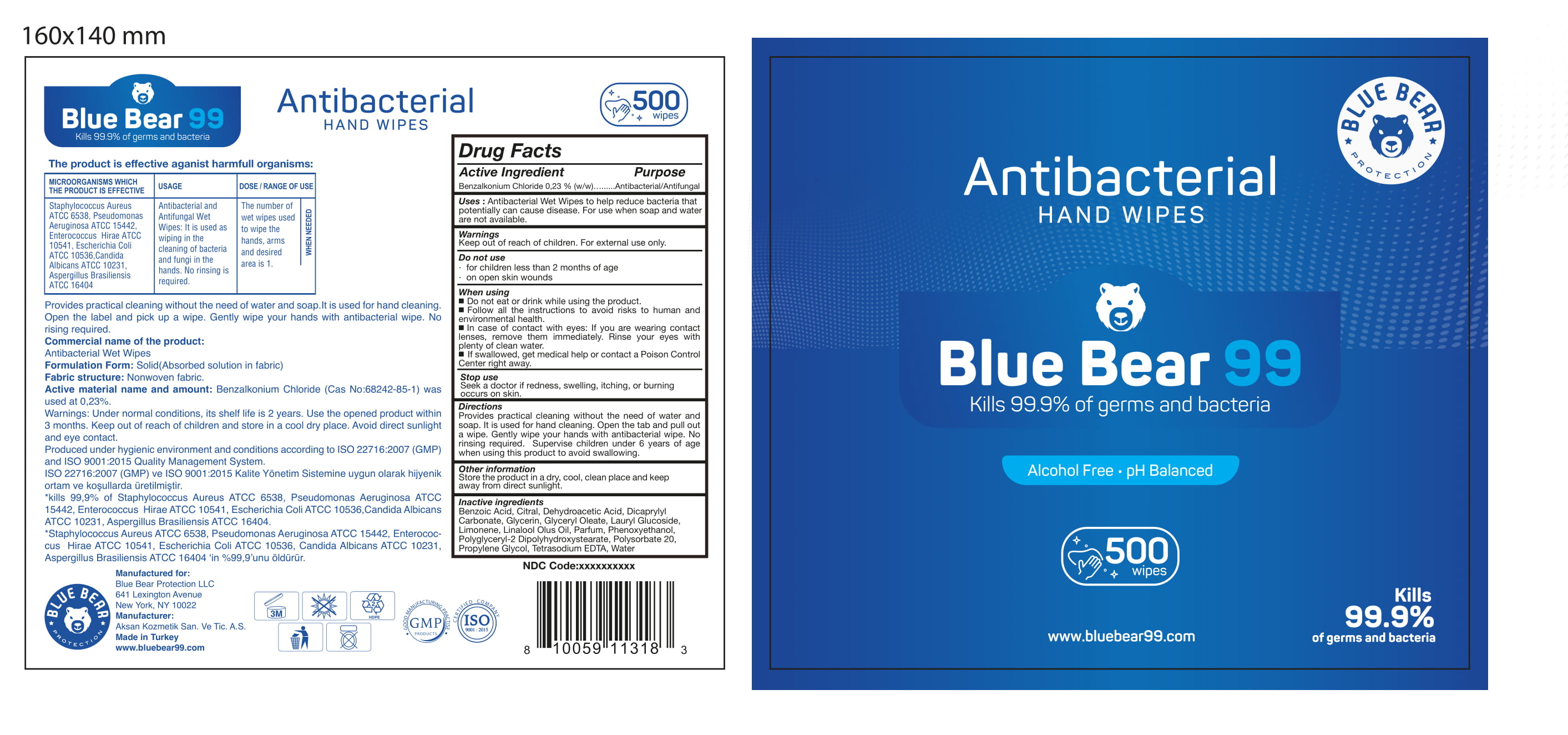 DRUG LABEL: Blue Bear Antibacterial Hand Wipes
NDC: 81005-001 | Form: CLOTH
Manufacturer: Blue Bear Protection LLC
Category: otc | Type: HUMAN OTC DRUG LABEL
Date: 20201208

ACTIVE INGREDIENTS: BENZALKONIUM CHLORIDE 0.23 g/100 g
INACTIVE INGREDIENTS: GLYCERIN; BENZOIC ACID; WATER; CITRAL; DEHYDROACETIC ACID; GLYCERYL OLEATE; LINALOOL, (+)-; PROPYLENE GLYCOL; ETIDRONATE TETRASODIUM; DICAPRYLYL CARBONATE; LAURYL GLUCOSIDE; LIMONENE, (+)-; FATTY-ACID AMIDE HYDROLASE 1; PHENOXYETHANOL; POLYGLYCERYL-2 DIPOLYHYDROXYSTEARATE; POLYSORBATE 20

Blue Bear Antibacterial Hand Wipes

The hand sanitizer is manufactured using only the following United States Pharmacopoeia (USP) grade ingredients in the preparation of the product (percentage in final product formulation) consistent with World Health Organization (WHO) recommendations:

1. Benzalkonium Chloride (0.23%, weight/weight (w/w)
2. Aqua,
3. Benzoic Acid,
4. Citral,
5. Dehydroacetic Acid,
6. Dicaprylyl Carbonate,
7. Glycerin,
8. Glyceryl Oleate,
9. Lauryl Glucoside,
10. Limonene,
11. Linalool
12. Olus Oil,
13. Parfum,
14. Phenoxyethanol,
15. Polyglyceryl-2 Dipolyhydroxystearate,
16. Polysorbate 20,
17. Propylene Glycol,
18. Tetrasodium EDTA

Active Ingredient(s)

Benzalkonium Chloride 0.23% w/w. Purpose: Antibacterial/ Antifungal

Purpose

Antibacterial / Antifungal, Hand Sanitizer

Use

Antibacterial Wet Wipes to help reduce bacteria that potentially can cause disease. For use when soap and water are not available.

Warnings

Keep out of reach of children. For external use only.

Do not use

- in children less than 2 months of age
- on open skin wounds

WHEN USING

Do not eat or drink while using the product. Follow all the instructions to avoid risks on human and environmental health. In case of contact with eyes:If you are wearing contact lenses,remove them immediately.Rinse your eyes with plenty of clean water.
Stop use and ask a doctor if irritation or rash occurs. These may be signs of a serious condition.
Keep out of reach of children. If swallowed, get medical help or contact a Poison Control Center right away.

STOP USE

Seek a doctor if redness, swelling, itching, or burning occurs on skin

Keep out of reach of children. If swallowed, get medical help or contact a Poison Control Center right away.

Directions

- Provides practical cleaning without the need of water and soap. It is used for hand cleaning. Open the label and pick up a wipe. Gently wipe your hands with antibacterial wipe. No rising required
- Supervise children under 6 years of age when using this product to avoid swallowing.

Other information

- Store the product dry, cool, clean place and keep away from direct sunlight

Inactive ingredients

Aqua, Benzoic Acid, Citral, Dehydroacetic Acid, Dicaprylyl Carbonate, Glycerin, Glyceryl Oleate, Lauryl Glucoside, Limonene, Linalool Olus Oil, Parfum, Phenoxyethanol, Polyglyceryl-2 Dipolyhydroxystearate, Polysorbate 20, Propylene Glycol, Tetrasodium EDTA